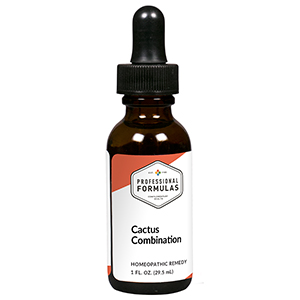 DRUG LABEL: Cactus Combination
NDC: 63083-9213 | Form: LIQUID
Manufacturer: Professional Complementary Health Formulas
Category: homeopathic | Type: HUMAN OTC DRUG LABEL
Date: 20190815

ACTIVE INGREDIENTS: HAWTHORN LEAF WITH FLOWER 2 [hp_X]/29.5 mL; SELENICEREUS GRANDIFLORUS STEM 3 [hp_X]/29.5 mL; POTASSIUM CARBONATE 3 [hp_X]/29.5 mL; SPIGELIA ANTHELMIA WHOLE 3 [hp_X]/29.5 mL; NITROGLYCERIN 6 [hp_X]/29.5 mL
INACTIVE INGREDIENTS: ALCOHOL; WATER

R213

ACTIVE INGREDIENTS

Crataegus oxyacantha 2X
Cactus grandiflorus 3X
Kali carbonicum 3X
Spigelia anthelmia 3X
Glonoinum 6X

QUESTIONS

Professional Formulas

PO Box 2034 Lake Oswego, OR 97035

INDICATIONS

For the temporary relief of muscle cramps or spasms, mild abdominal or chest pain, or anxiousness.*

PURPOSE

*Claims based on traditional homeopathic practice, not accepted medical evidence. Not FDA evaluated.

WARNINGS

Seek medical attention immediately for severe symptoms such as chest pressure or tightness with radiation of the pain to the jaw and down the arm, shortness of breath, or sweating. Keep out of the reach of children. In case of overdose, get medical help or contact a poison control center right away. If pregnant or breastfeeding, ask a healthcare professional before use.

Keep out of the reach of children.

PREGNANCY OR BREAST FEEDING

If pregnant or breastfeeding, ask a healthcare professional before use.

DIRECTIONS

Place drops under tongue 30 minutes before/after meals. Adults and children 12 years and over: Take 10 drops up to 3 times per day. Consult a physician for use in children under 12 years of age.

OTHER INFORMATION

Tamper resistant. If seal is broken, do not use. After opening, close container tightly and store at room temperature away from heat.

INACTIVE INGREDIENTS

40% ethanol, purified water.

LABEL

Est 1985

Professional Formulas

Complementary Health

Cactus Combination

Homeopathic Remedy

1 FL. OZ. (29.5 mL)